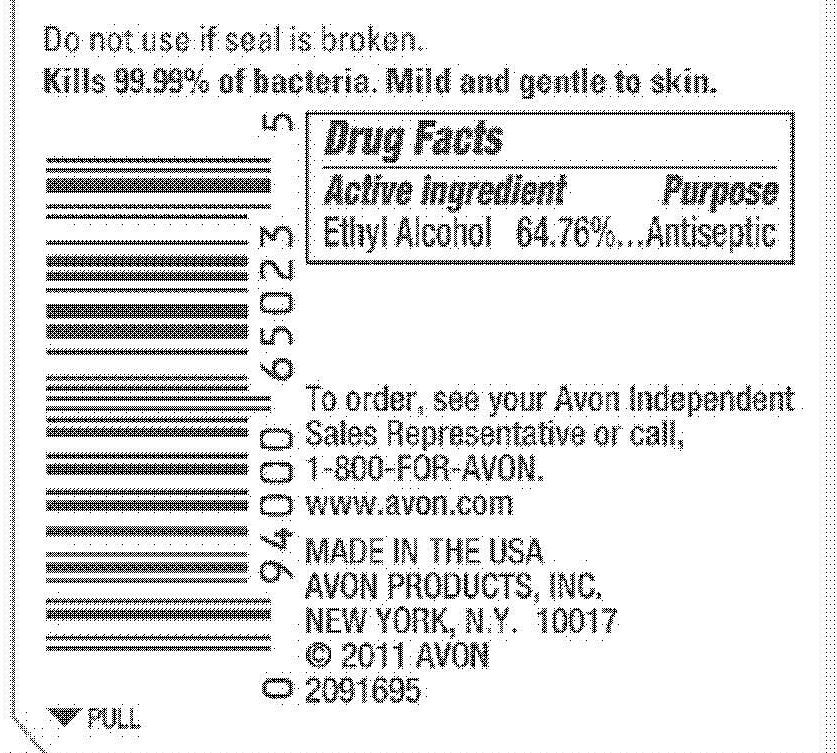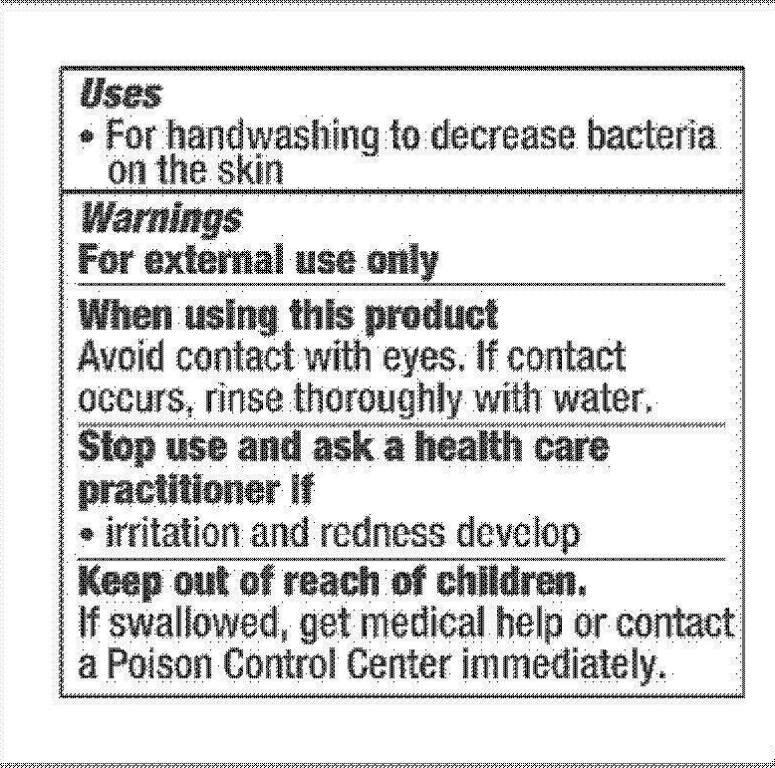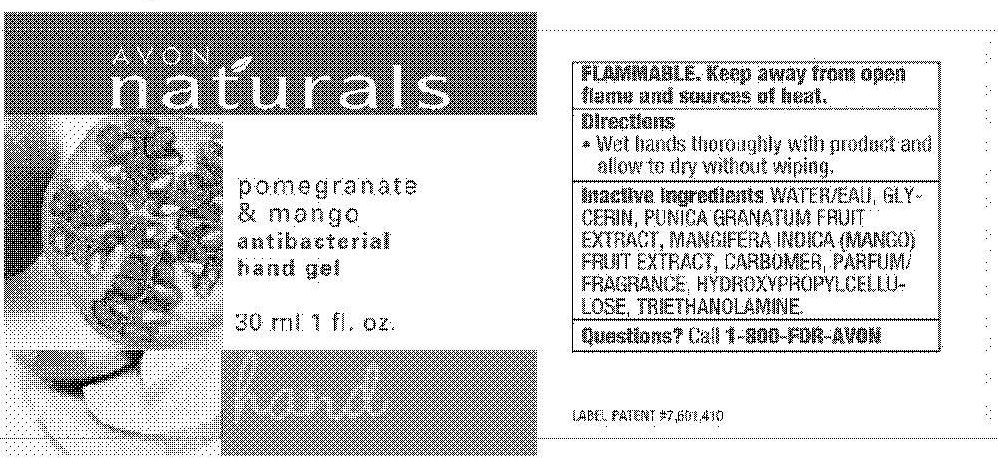 DRUG LABEL: Naturals
NDC: 10096-0252 | Form: GEL
Manufacturer: New Avon LLC
Category: otc | Type: HUMAN OTC DRUG LABEL
Date: 20190101

ACTIVE INGREDIENTS: ALCOHOL	 19.428 mL/30 mL
INACTIVE INGREDIENTS: WATER

Naturals Pomegranate Mango Antibacterial Hand Gel

Active Ingredient
Ethyl Alcohol 64.76%.......................

Purpose
...............Antiseptic

Uses

- For handwashing to decrease bacteria on the skin

Warnings
For external use only

When using this product

Avoid contact with eyes. If contact occurs, rinse thoroughly with water.

Stop use and ask a health care practitioner if

- irritation and redness develop

Keep out of reach of children. If swallowed, get medical help or contact a Poison Control Center immediately.

GENERAL PRECAUTIONS

FLAMMABLE. Keep away from open flame and sources of heat.

Directions

- Wet hands thoroughly with product and allow to dry without wiping.

Inactive ingredients

WATER/EAU
GLYCERIN
PUNICA GRANATUM FRUIT EXTRACT
MANGIFERA INDICA (MANGO) FRUIT EXTRACT
CARBOMER
PARFUM/FRAGRANCE
HYDROXYPROPYLCELLULOSE
TRIETHANOLAMINE

Questions? Call 1-800-FOR-AVON